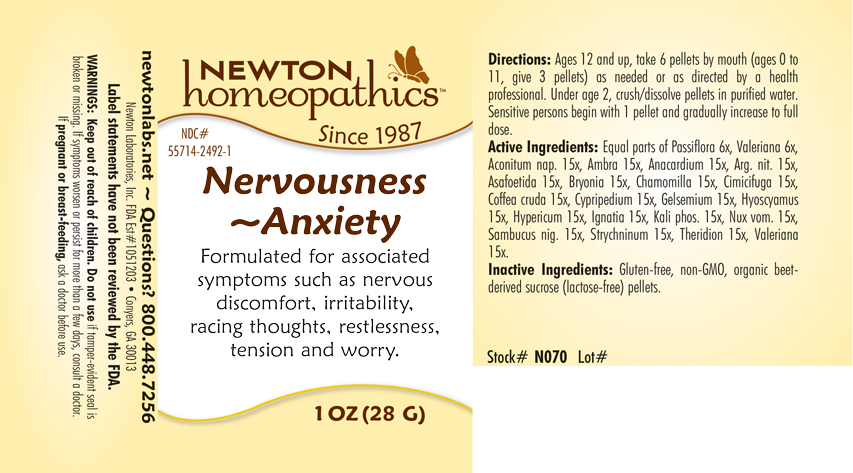 DRUG LABEL: Nervousness - Anxiety
NDC: 55714-2492 | Form: PELLET
Manufacturer: Newton Laboratories, Inc.
Category: homeopathic | Type: HUMAN OTC DRUG LABEL
Date: 20250207

ACTIVE INGREDIENTS: ACONITUM NAPELLUS 15 [hp_X]/1 g; AMBERGRIS 15 [hp_X]/1 g; SEMECARPUS ANACARDIUM JUICE 15 [hp_X]/1 g; SILVER NITRATE 15 [hp_X]/1 g; FERULA ASSA-FOETIDA RESIN 15 [hp_X]/1 g; BRYONIA ALBA ROOT 15 [hp_X]/1 g; MATRICARIA CHAMOMILLA 15 [hp_X]/1 g; BLACK COHOSH 15 [hp_X]/1 g; ARABICA COFFEE BEAN 15 [hp_X]/1 g; CYPRIPEDIUM PARVIFLORUM VAR. PUBESCENS ROOT 15 [hp_X]/1 g; GELSEMIUM SEMPERVIRENS ROOT 15 [hp_X]/1 g; HYOSCYAMUS NIGER 15 [hp_X]/1 g; HYPERICUM PERFORATUM 15 [hp_X]/1 g; STRYCHNOS IGNATII SEED 15 [hp_X]/1 g; DIBASIC POTASSIUM PHOSPHATE 15 [hp_X]/1 g; STRYCHNOS NUX-VOMICA SEED 15 [hp_X]/1 g; SAMBUCUS NIGRA FLOWERING TOP 15 [hp_X]/1 g; STRYCHNINE 15 [hp_X]/1 g; THERIDION CURASSAVICUM 15 [hp_X]/1 g; VALERIAN 15 [hp_X]/1 g; PASSIFLORA INCARNATA FLOWERING TOP 6 [hp_X]/1 g
INACTIVE INGREDIENTS: SUCROSE

Nervousness 2492P

INDICATIONS & USAGE SECTION

Formulated for associated symptoms such as nervous discomfort, irritability, racing thoughts, restlessness, tension and worry.

DOSAGE & ADMINISTRATION SECTION

Directions: Ages 12 and up, take 6 pellets by mouth (ages 0 to 11, give 3 pellets) as needed or as directed by a health professional. Under age 2, crush/dissolve pellets in purified water. Sensitive persons begin with 1 pellet and gradually increase to full dose.

OTC - ACTIVE INGREDIENT SECTION

Equal parts of Passiflora incarnata 6x, Valeriana officinalis 6x, Aconitum napellus 15x, Ambra grisea 15x, Anacardium orientale 15x, Argentum nitricum 15x, Asafoetida 15x, Bryonia 15x, Chamomilla 15x, Cimicifuga racemosa 15x, Coffea cruda 15x, Cypripedium pubescens 15x, Gelsemium sempervirens 15x, Hyoscyamus niger 15x, Hypericum perforatum 15x, Ignatia amara 15x, Kali phosphoricum 15x, Nux vomica 15x, Sambucus nigra 15x, Strychninum 15x, Theridion 15x, Valeriana officinalis 15x.

OTC - PURPOSE SECTION

Formulated for associated symptoms such as nervous discomfort, irritability, racing thoughts, restlessness, tension and worry.

INACTIVE INGREDIENT SECTION

Inactive Ingredients: Gluten-free, non-GMO, organic beet-derived surose (lactose-free) pellets.

QUESTIONS SECTION

newtonlabs.net – Questions? 800.448.7256

Newton Laboratories, Inc. FDA Est # 1051203 - Conyers, GA 30013

WARNINGS SECTION

WARNINGS: Keep out of reach of children. Do not use if tamper-evident seal is broken or missing. If symptoms worsen or persist for more than a few days, consult a doctor. If pregnant or breast-feeding, ask a doctor before use.

OTC - PREGNANCY OR BREAST FEEDING SECTION

If pregnant or breast-feeding, ask a doctor before use.

OTC - KEEP OUT OF REACH OF CHILDREN SECTION

Keep out of reach of children.